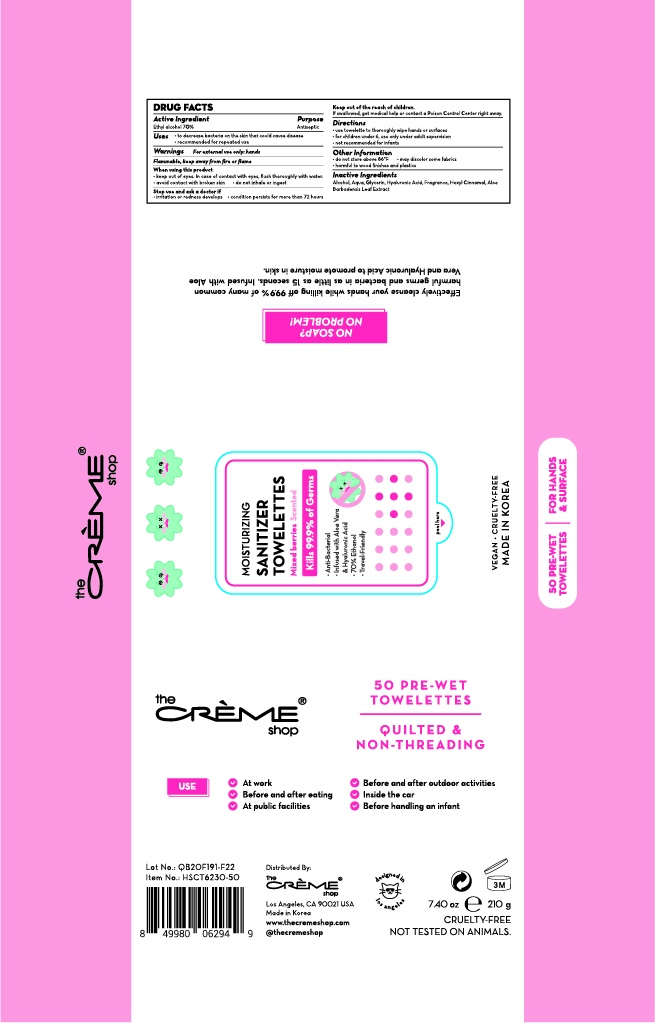 DRUG LABEL: The creme shop Moisturizing Sanitizer Towelettes Mixed Berries Scented
NDC: 74741-7208 | Form: CLOTH
Manufacturer: MPRBRAIN CO.LTD
Category: otc | Type: HUMAN OTC DRUG LABEL
Date: 20200616

ACTIVE INGREDIENTS: ALCOHOL 0.7 g/1 1
INACTIVE INGREDIENTS: .ALPHA.-HEXYLCINNAMALDEHYDE; ALOE VERA LEAF; GLYCERIN; HYALURONIC ACID; WATER

The creme shop Moisturizing Sanitizer Towelettes Mixed Berries Scented : 50 Towelettes
74741-7208-1